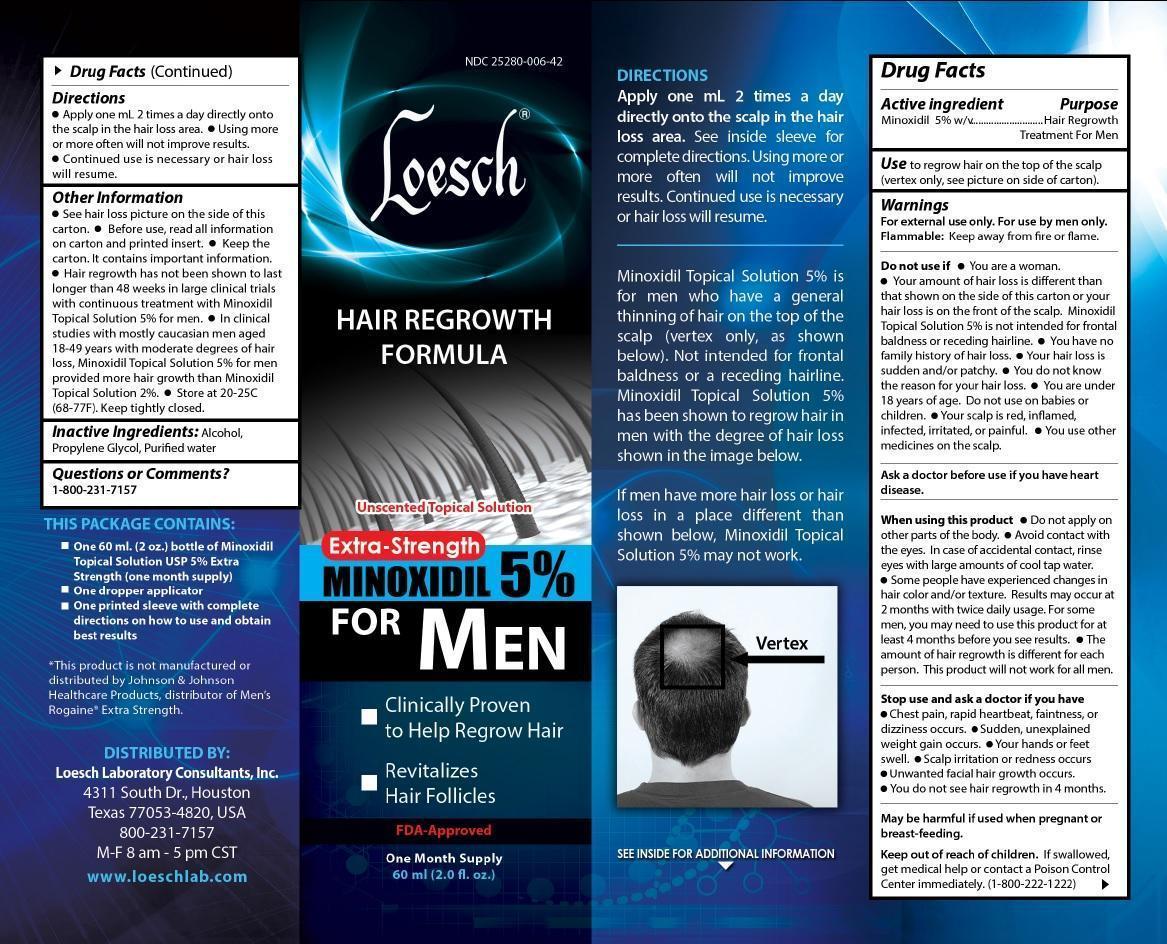 DRUG LABEL: Loesch Hair Regrowth Formula
NDC: 25280-006 | Form: SOLUTION
Manufacturer: Loesch Laboratory Consultant, INC.
Category: otc | Type: HUMAN OTC DRUG LABEL
Date: 20251203

ACTIVE INGREDIENTS: MINOXIDIL 3 g/60 mL
INACTIVE INGREDIENTS: WATER; PROPYLENE GLYCOL; ALCOHOL

Active Ingredients

Minoxidil 5% w/v

Purpose

Hair Regrowth Treatment For Men

Use

to regrow hair on the top of the scalp (vertex only, see pictures on side of carton).

Warnings

For external use only. Flammable: Keep away from fire or flame.

Do not use if

You are a woman

Your amount of hair loss is different than that shown on the side of this carton or your hair loss is on the front of the scalp. Minoxidil Topical Solution 5% is not intended for frontal baldness or receding hairline.
You have no family history of hair loss.
Your hair loss is sudden and/or patchy.
You do not know the reason for your hair loss.
You are under 18 years of age. Do not use on babies or children.
Your scalp is red, inflamed, infected, irritated, or painful.
You use other medicines on the scalp.

ASK DOCTOR

Ask a doctor before use if you have heart disease.

When using this product

Do not apply on other parts of the body.
Avoid contact with the eyes. In case of accidental contact, rinse eyes with large amounts of cool tap water.
Some people have experienced changes in hair color and/or texture. Results may occur at 2 months with twice daily usage. For some men, you may need to use this product for at least 4 months before you see results.
The amount of hair regrowth is different for each person. This product will not work for everyone.

Stop use and ask a doctor if you have

Chest pain, rapid heartbeat, faintness, or dizziness occurs.
Sudden, unexplained weight gain occurs.
Your hands or feet swell.
Scalp irritation or redness occurs.
Unwanted facial hair growth occurs.
You do not see hair regrowth in 4 months.

Pregnancy or breast feeding

May be harmful if used when pregnant or breast-feeding.

Keep out of reach of children

If swallowed, get medical help or contact a Poison Control Center immediately. (1-800-222-1222)

Directions

Apply one mL 2 times daily directly onto the scalp in the hair loss area.
Using more or more often will not improve results.
Continued use is necessary or hair loss will resume.

Other information

See hair loss picture on the side of this carton.
Before use, read all information on carton and printed insert.
Keep the carton. It contains important information.
Hair regrowth has not been shown to last longer than 48 weeks in large clinical trials with continuous treatment with Minoxidil Topical Solution 5%.
In clinical studies with mostly caucasian men aged 18-49 years with moderate degrees of hair loss, Minoxidil Topical Solution 5% for men provided more hair growth than Minoxidil Topical Solution 2%.

Inactive Ingredients

Alcohol, Propylene Glycol, Purified water

Questions or Comments?

1-800-237-7157